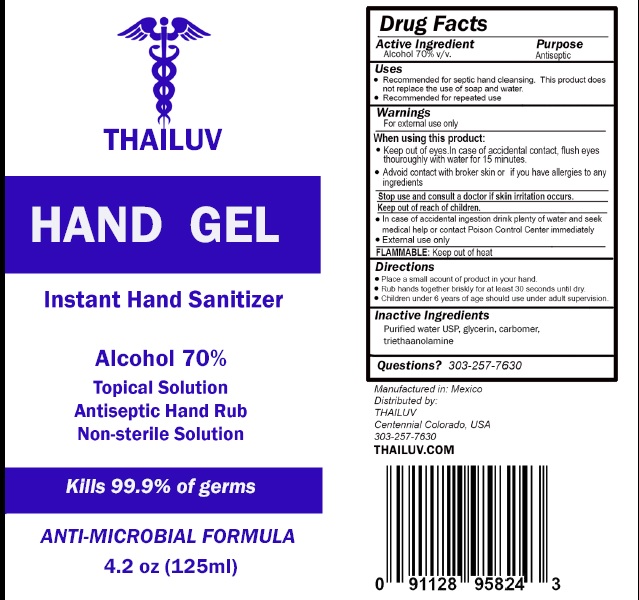 DRUG LABEL: THAILUV
NDC: 78101-001 | Form: GEL
Manufacturer: THAILUV LLC
Category: otc | Type: HUMAN OTC DRUG LABEL
Date: 20200520

ACTIVE INGREDIENTS: ALCOHOL 70 mL/100 mL
INACTIVE INGREDIENTS: CARBOMER 940; TRIETHANOLAMINE HYDRIODIDE; GLYCERIN; WATER

THAILUV

Active Ingredient

Alcohol 70%

Purpose

Antiseptic

Uses

- Recommended for septic hand cleansing. This product does not replace the use of soap and water.
- Recommended for repeated use

Warnings

For external use only.

When using this product:
• Keep out of eyes .ln case of accidental contact, flush eyes thouroughly with water for 15 m1nutes.
• Advoid contact with broker skin or if you have allergies to any ing redients

Stop use and consult a doctor if skin irritation occurs

Keep out of reach of children

- In case of accidental ingestion drink plenty of water and seek medical help or contact Poison Control Center immediately
- External use only

FLAMMABLE: Keep out of heat

Directions

- Place a small acount of product in your hand.
- Rub hands together briskly for at least 30 seconds until dry.
- Children under 6 years of age should use under adult supervision

Questions? 303-257-7630

Inactive Ingredients

Purified water USP, glycerin, carbomer, triethaanolamine